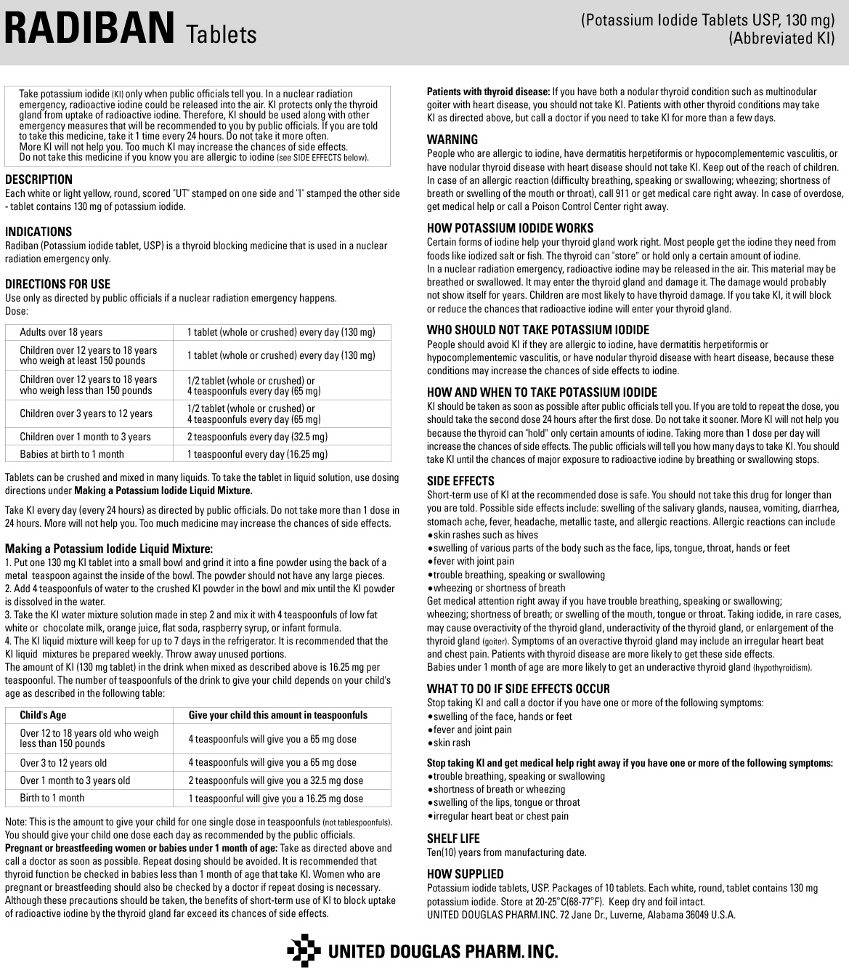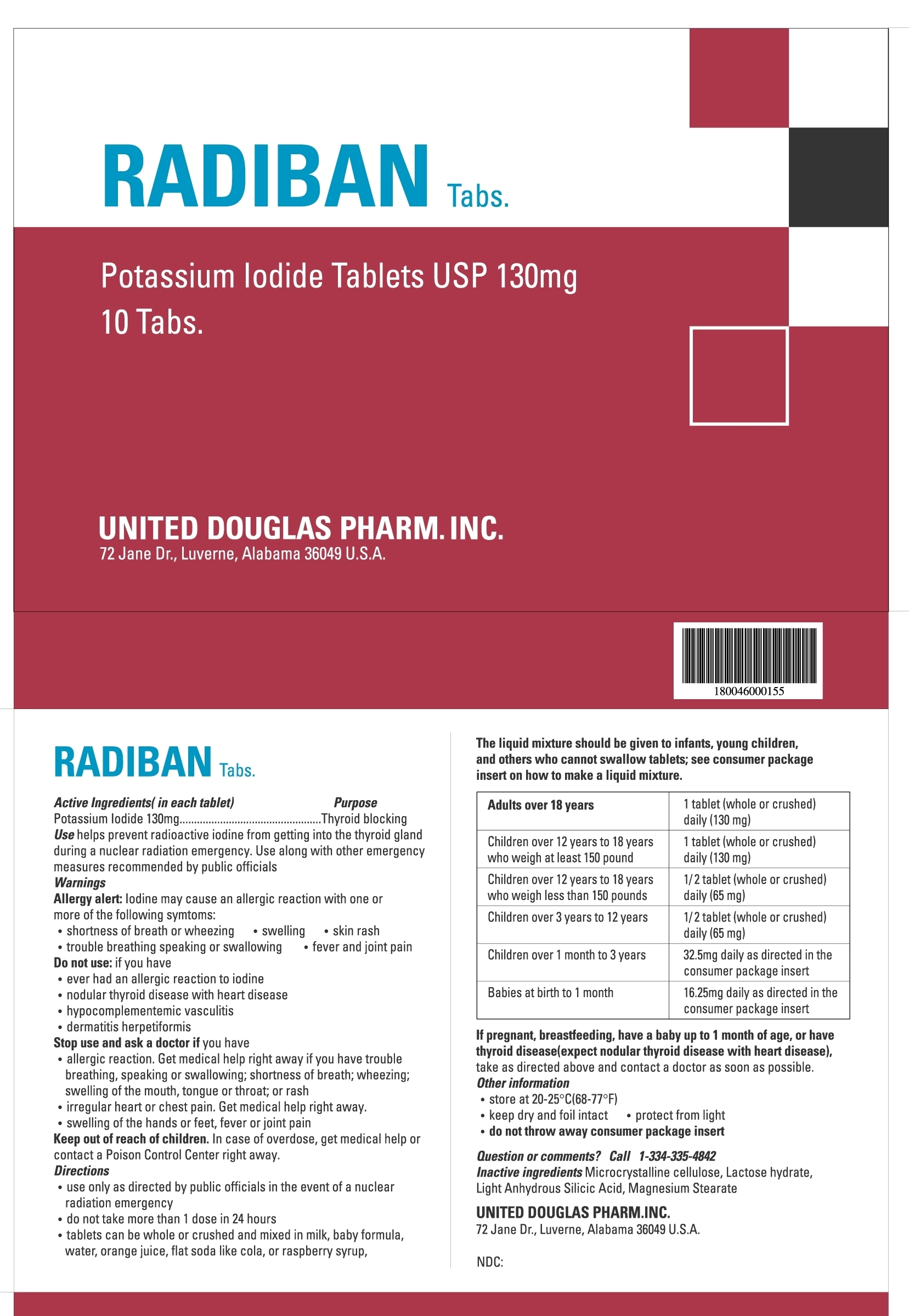 DRUG LABEL: Radiban
NDC: 65697-513 | Form: TABLET
Manufacturer: United Douglas Pharm., Inc.
Category: otc | Type: HUMAN OTC DRUG LABEL
Date: 20111221

ACTIVE INGREDIENTS: Potassium Iodide 130 mg/1 1
INACTIVE INGREDIENTS: Cellulose, Microcrystalline; Lactose Monohydrate; Silicon Dioxide; Magnesium Stearate

Active Ingredient (in each tablet) .... Potassium Iodide 130 mg.

Purpose --- Thyroid Blocking

Use --- Potassium iodide helps prevent radioactive iodine from getting into the thyroid gland during a nuclear radiation emergency. Use along with other emergency measures recommended by public officials.

Keep out of reach of children.

INDICATIONS AND USAGE

Radiban (Potassium iodide tablet, USP) is a thyroid blocking medicine that helps prevent radioactive iodine from getting into the thyroid gland during a nuclear radiation emergency. Use along with other emergency measures recommended by public officials. Radiban is to be used only in the case of a nuclear radiation emergency. It is not for everyday use. Because of the stability of potassium iodide, the shelf life for Radiban is 10 years.

Allergy Alert: Iodine may cause an allergic reaction with one or more of the following symptoms:

- Shortness of breath or wheezing
- Swelling
- Skin rash
- Trouble breathing, speaking, or swallowing
- Fever and joint pain

Do not use if you have:

- Ever had an allergic reaction to iodine
- Nodular thyroid disease with heart disease
- Hypocomplementemic vasculitis
- Dermatitis herpetiformis

Stop use and ask doctor if you have:

- Allergic reaction. Get medical help right away if you have trouble breathing, speaking, or swallowing; shortness of breath; wheezing; swelling of the mouth, tongue, or throat; or rash.
- Irregular heartbeat or chest pain. Get help right away.
- Swelling of the hands or feet, fever, or joint pain.

Directions

- Use only as directed by public officials in the event of a nuclear radiation emergency.
- Do not take more than 1 dose in 24 hours.
- Tablets can be whole or crushed and mixed with milk, water, orange juice, flat soda like cola, or raspberry syrup.

Dosage:

Adults over 18 years ........................................................................... 1 tablet (whole or crushed) daily (130 mg)

Children over 12 years to 18 years who weigh at least 150 pounds .......... 1 Tablet (whole or crushed) daily (130 mg)

Children over 12 years to 18 years who weigh less than 150 pounds ....... 1/2 Tablet (whole or crushed) or 4 teaspoons of liquid mix daily (65 mg)

Children over 3 years to 12 years ........................................................ 1/2 Tablet (whole or crushed) or 4 teaspoons of liquid mix daily (65 mg)

Children over 1 month to 3 years ......................................................... 2 teaspoons of liquid mix daily (32.5 mg)

Infants at birth to 1 month ................................................................... 1 teaspoon of liquid mix daily (16.25 mg)

The liquid mixture should be given to infants, young children, and any others who cannot swallow tablets; see consumer package insert on how to make a liquid mixture.

INACTIVE INGREDIENT

Inactive Ingredients: Microcrystalline cellulose, Lactose hydrate, Light Anhydrous Silicic Acid, Magnesium Stearate

Radiban Label Text

PATIENT INFORMATION

Radiban Insert text